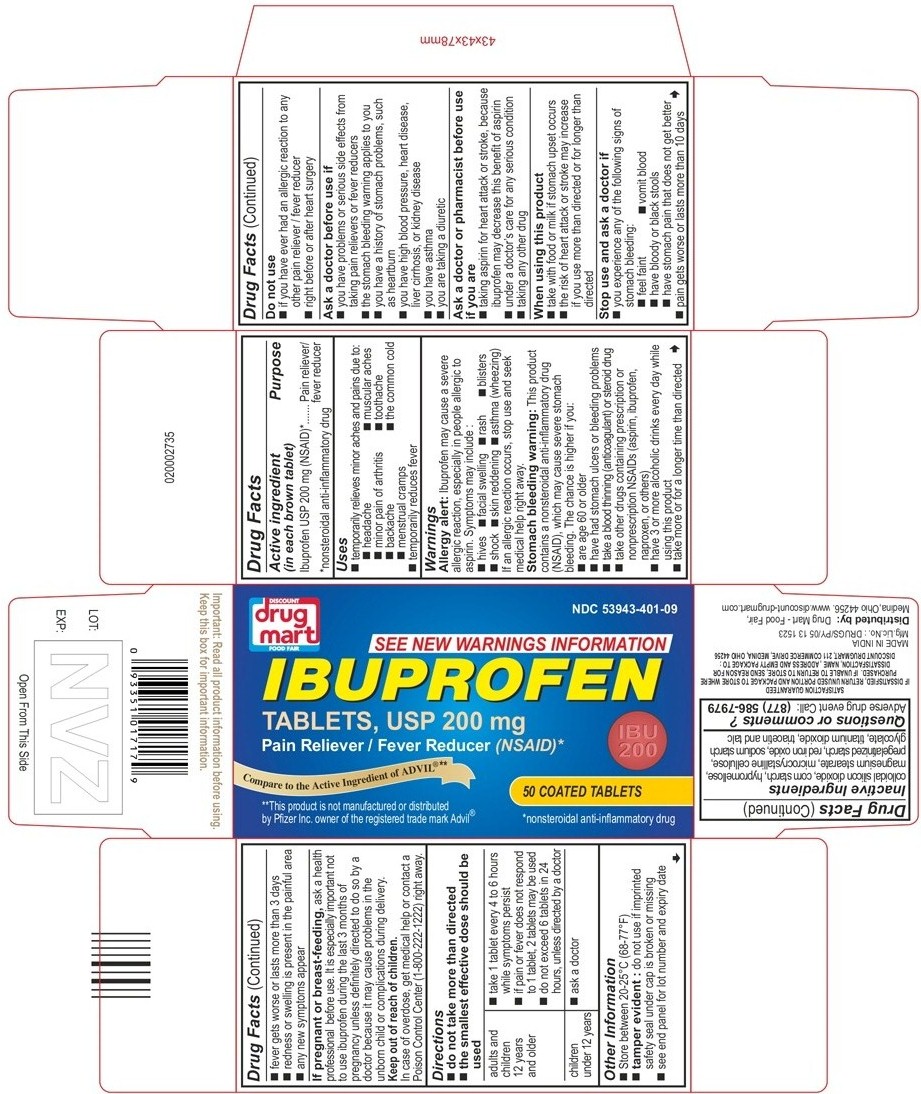 DRUG LABEL: IBUPROFEN
NDC: 53943-401 | Form: TABLET, COATED
Manufacturer: Discount Drug Mart
Category: otc | Type: Human OTC Drug Label
Date: 20141118

ACTIVE INGREDIENTS: IBUPROFEN 200 mg/1 1
INACTIVE INGREDIENTS: COLLOIDAL SILICON DIOXIDE; MAGNESIUM STEARATE; CELLULOSE, MICROCRYSTALLINE; STARCH, PREGELATINIZED CORN; SODIUM STARCH GLYCOLATE TYPE A POTATO; HYPROMELLOSE 2910 (6 MPA.S); TITANIUM DIOXIDE; TRIACETIN; TALC; FERRIC OXIDE RED

Ibuprofen tablets USP 200mg
Discount Drug Mart
Drug Facts

ACTIVE INGREDIENT(S)

(in each brown tablet)
Ibuprofen USP 200 mg (NSAID)*
*nonsteroidal anti-inflammatory drug

PURPOSE

Pain reliever/fever reducer

USE(S)

- temporarily relieves minor aches and pains due to:
  - headache
  - muscular aches
  - minor pain of arthritis
  - toothache
  - backache
  - the common cold
  - menstrual cramps
- temporarily reduces fever

WARNINGS

Allergy alert

Ibuprofen may cause a severe allergic reaction, especially in people allergic to aspirin. Symptoms may include:

- hives
- facial swelling
- asthma (wheezing)
- shock
- skin reddening
- rash
- blisters

If an allergic reaction occurs, stop use and seek medical help right away.

Stomach bleeding warning

This product contains an nonsteroidal anti-inflammatory drug (NSAID), which may cause severe stomach bleeding. The chance is higher if you:

- are age 60 or older
- have had stomach ulcers or bleeding problems
- take a blood thinning (anticoagulant) or steroid drug
- take other drugs containing prescription or nonprescription NSAIDs (aspirin, ibuprofen, naproxen, or others)
- have 3 or more alcoholic drinks every day while using this product
- take more or for a longer time than directed

DO NOT USE

- if you have ever had an allergic reaction to any other pain reliever / fever reducer
- right before or after heart surgery

ASK A DOCTOR BEFORE USE IF

- you have problems or serious side effects from taking pain relievers or fever reducers
- the stomach bleeding warning applies to you
- you have a history of stomach problems, such as heartburn
- you have high blood pressure, heart disease, liver cirrhosis, or kidney disease
- you have asthma
- you are taking a diuretic

ASK A DOCTOR OR PHARMACIST BEFORE USE IF

- taking aspirin for heart attack or stroke, because ibuprofen may decrease this benefit of aspirin
- under a doctor’s care for any serious condition
- taking any other drug

WHEN USING THIS PRODUCT

- take with food or milk if stomach upset occurs
- the risk of heart attack or stroke may increase if you use more than directed or for longer than directed

STOP USE AND ASK DOCTOR IF

- you experience any of the following signs of stomach bleeding
  - feel faint
  - vomit blood
  - have bloody or black stools
  - have stomach pain that does not get better
- pain gets worse or lasts more than 10 days
- fever gets worse or lasts more than 3 days
- redness or swelling is present in the painful area
- any new symptoms appear

If pregnant or breast-feeding, ask a health professional before use. It is especially important not to use ibuprofen during the last 3 months of pregnancy unless definitely directed to do so by a doctor because it may cause problems in the unborn child or complications during delivery.

KEEP OUT OF REACH OF CHILDREN

In case of overdose, get medical help or contact a poison control center (1-800-222-1222) right away.

DIRECTIONS

• do not take more than directed
• the smallest effective dose should be used

adults and children 12 years and older | - take 1 tablet every 4 to 6 hours while symptoms persist - if pain or fever does not respond to 1 tablet, 2 tablets may be used - do not exceed 6 tablets in 24 hours, unless directed by a doctor
children under 12 years | • ask a doctor

OTHER INFORMATION

- store between 20 – 25°C (68-77°F)
- tamper evident: do not use if imprinted safety seal under cap is broken or missing
- see end panel for lot number and expiry date

INACTIVE INGREDIENT (S)

colloidal silicon dioxide, corn starch, hypromellose, magnesium stearate, microcrystalline cellulose, pregelatinized starch, red iron oxide, sodium starch glycolate, titanium dioxide, triacetin and talc

QUESTIONS OR COMMENTS?
Adverse drug event Call: (877) 586-7979

PRINCIPAL DISPLAY PANEL

Package Label (Round Shaped Tablets) - Principal Display Panel - 50s - Count Carton, 200 mg Tablets

DISCOUNT
drug mart
FOOD FAIR
NDC 53943-401-09
SEE NEW WARNINGS INFORMATION
IBUPROFEN
TABLETS, USP 200 mg
Pain Reliever / Fever Reducer (NSAID)*
IBU
200
50 COATED TABLETS
*nonsteroidal anti-inflammatory drug
Compare to the Active Ingredient of ADVIL@**
**This product is not manufactured or distributed by Pfizer Inc. owner of the registered trade mark Advil@